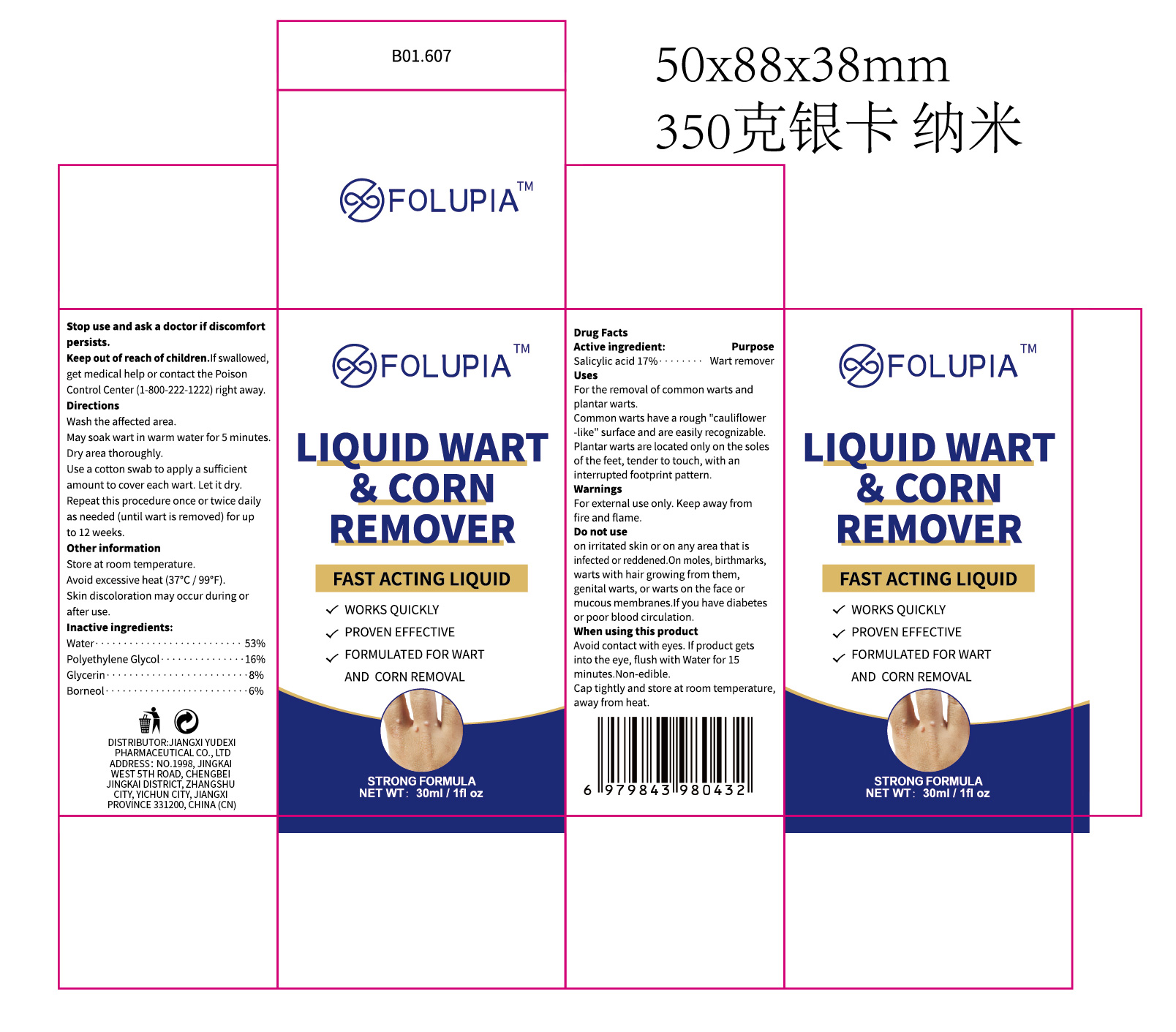 DRUG LABEL: FOLUPIA  Liquid WART CORN REMOVER
NDC: 85248-149 | Form: LIQUID
Manufacturer: Jiangxi Yudexi Pharmaceutical Co., LTD
Category: otc | Type: HUMAN OTC DRUG LABEL
Date: 20260227

ACTIVE INGREDIENTS: SALICYLIC ACID 17 g/100 mL
INACTIVE INGREDIENTS: WATER; BORNEOL; POLYETHYLENE GLYCOL, UNSPECIFIED; GLYCERIN

85248-149

Active Ingredient

Salicylic acid 17%

Purpose

Wart remover

Use

For the removal of common warts and plantar warts.Common warts have a rough"cauliflower-like" surface and are easily recognizable.Plantar warts are located only on the soles of the feet, tender to touch, with an interrupted footprint pattern.

Warnings

For external use only. Keep away from fire and flame.

Do not use

on irritated skin or on any area that is infected or reddened.On moles, birthmarks,warts with hair growing from them, genital warts, or warts on the face or mucous membranes.lf you have diabetes or poor blood circulation.

When Using

Avoid contact with eyes. lf product gets into the eye, flush with Water for 15 minutes.Non-edible.Cap tightly and store at room temperature,away from heat.

Stop Use

Stop use and ask a doctor if discomfort persists.

Ask Doctor

Stop use and ask a doctor if discomfort persists.

Keep Oot Of Reach Of Children

lf swallowed, get medical help or contact the Poison Control Center(1-800-222-1222)right away.

Directions

Wash the affected area. May soak wart in warm water for 5 minutes.Dry area thoroughly. Use a cotton swab to apply a sufficient amount to cover each wart. Let it dry. Repeat this procedure once or twice daily as needed (until wart is removed) for upto 12 weeks.

Other information

Store at room temperature.Avoid excessive heat (37°C/99°F).Skin discoloration may occur during or after use.

Inactive ingredients

Water,Polyethylene Glycol,Glycerin,Borneol.